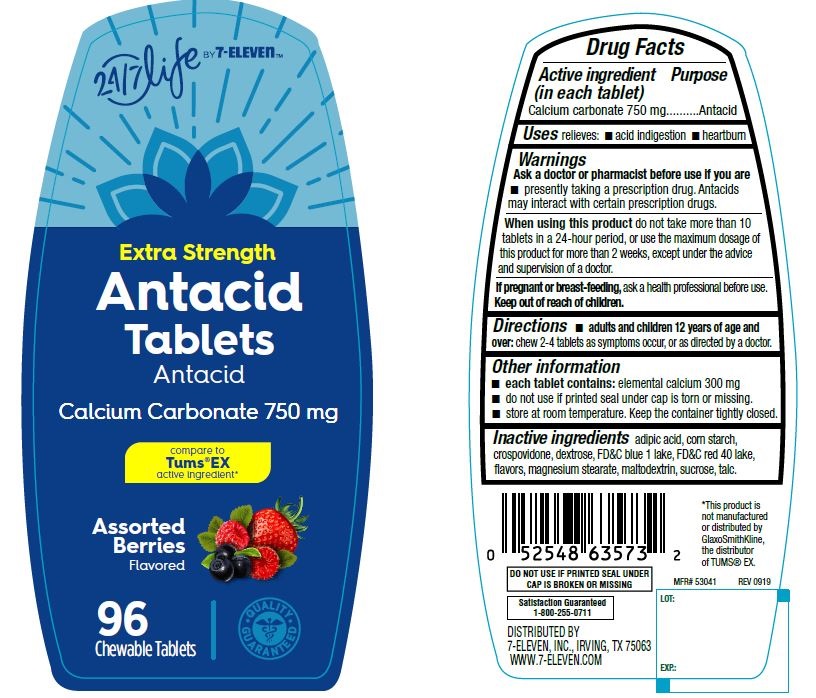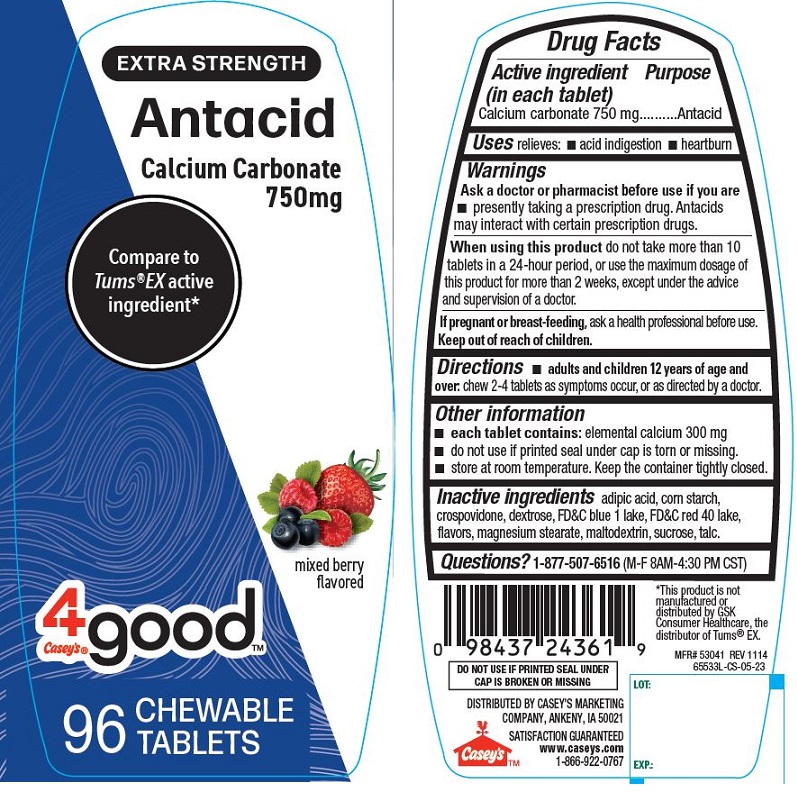 DRUG LABEL: Extra Strength Antacid Tablets, Caseys 4good
NDC: 66715-6355 | Form: TABLET, CHEWABLE
Manufacturer: Lil' Drug Store Prodsucts, Inc.
Category: otc | Type: HUMAN OTC DRUG LABEL
Date: 20241216

ACTIVE INGREDIENTS: CALCIUM CARBONATE 750 mg/1 1
INACTIVE INGREDIENTS: ADIPIC ACID; STARCH, CORN; CROSPOVIDONE; MAGNESIUM STEARATE; DEXTROSE; FD&C RED NO. 40; MALTODEXTRIN; SUCROSE; TALC; FD&C BLUE NO. 1 ALUMINUM LAKE

Antacid Tablets

Active Ingredient

Active ingredient (in each tablet)

Calcium carbonate 750 mg

Purpose

Antacid

Warnings

Ask a doctor or pharmacist before use if you are

- presently taking a prescription drug. Antacids may interact with certain prescription drugs.

When using this product do not take more than 10 tablets in a 24-hour period, or use the maximum dosage of this product for more than 2 weeks, except under the advice and supervision of a doctor.

PREGNANCY OR BREAST FEEDING

If pregnant or breast-feeding, ask a health professional before use.

Keep out of reach of children.

Uses

Uses relieves:

- acid indigestion
- heartburn

Directions

- adults and children 12 years of age and over: chew 2-4 tablets as symptoms occur, or as directed by a doctor.

Other information

- each tablet contains: elemental calcium 300 mg
- do not use if printed seal under cap is torn or missing.
- store at room temperature. Keep the container tightly closed.

Inactive ingredients

adipic acid, corn starch, crospovidone, dextrose, FD&C blue 1 lake, FD&C red 40 lake, flavors, magnesium stearate, maltodextrin, sucrose, talc.

PDP/Package Label, 24/7 Life Antacid Tablets

24/7 Life by 7-Eleven

Extra Strength

Antacid

Tablets

Antacid

Calcium Carbonate 750 mg

compare to

Tums® EX

active ingredient

Assorted

Berries

Flavored

96

Chewable Tablets

PDP/Package Label, Casey's 4good Antacid

EXTRA STRENGTH

Antacid

Calcium Carbonate

750 mg

Compare to

Tums® EX active

ingredient*

mixed berry

flavored

4goodTM

Casey's®

96 CHEWABLE

TABLETS